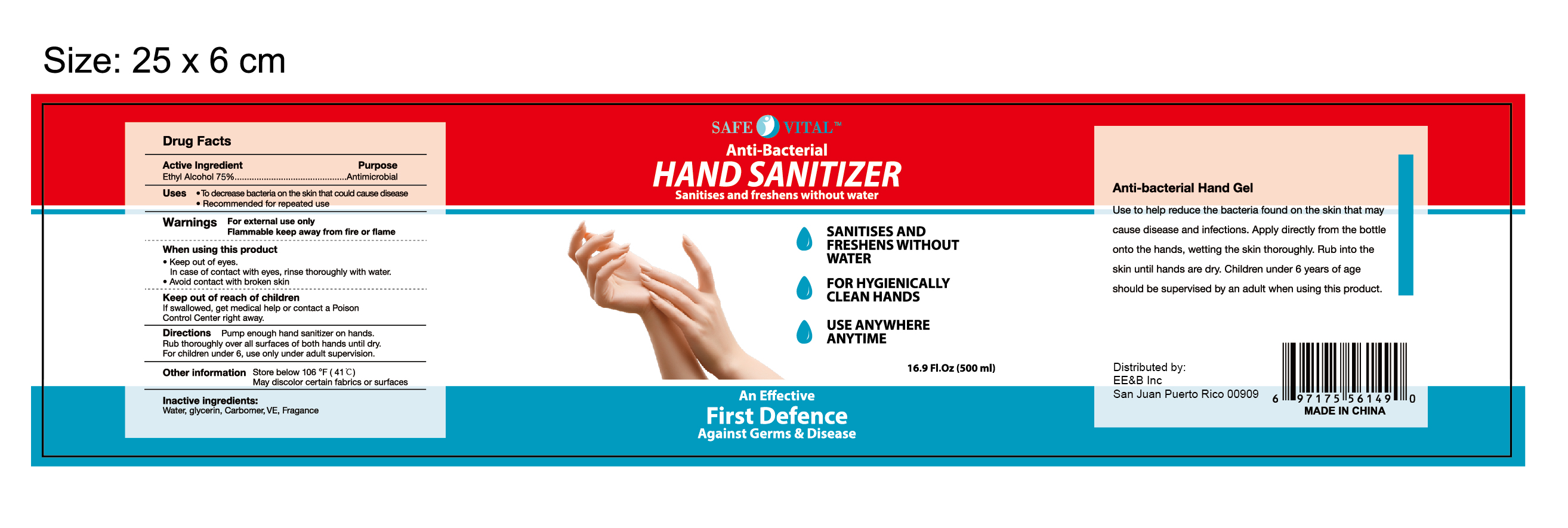 DRUG LABEL: Safe Vital Antibacterial Hand Sanitizer
NDC: 75236-002 | Form: GEL
Manufacturer: PUJIANG SHIJIALI COSMETICS CO., LTD.
Category: otc | Type: HUMAN OTC DRUG LABEL
Date: 20200506

ACTIVE INGREDIENTS: ALCOHOL 75 mL/100 mL
INACTIVE INGREDIENTS: GLYCERIN; WATER; CARBOMER 934; TOCOPHEROL

Active Ingredient(s)

Ethyl Alcohol 75%

Purpose

Antimicrobial

Use

To reduce bacteria on the skin that could cause disease

Recommended for repeated use

Warnings

For external use only -hands

Flammable. Keep away from fire or flame

When using this product keep out of eyes. In case of contact with eyes, rinse thoroughly with water.

Avoid contact with broken skin

Keep out of reach of children. If swallowed, get medical help or contact a Poison Control Center right away.

Directions

- Pump enough hand sanitizer on hands. Rub thoroughly over all surfaces of both hands until dry
- For children under 6, use only under adult supervision

Other information

Store below 106F (41C)

May discolor certain fabrics or surfaces

Inactive ingredients

Water, glycerin, carbomer, VE, fragrance